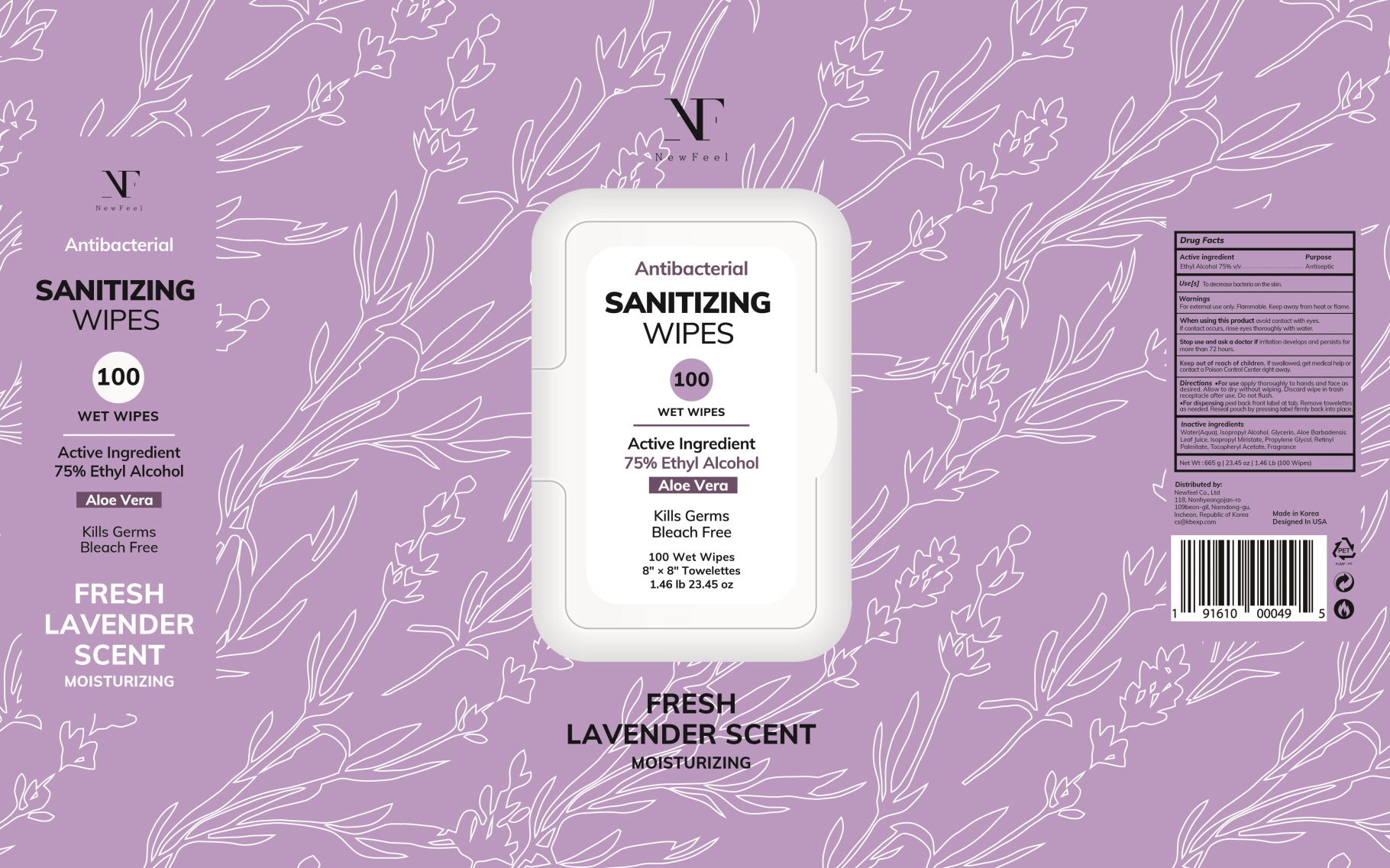 DRUG LABEL: Newfeel Antibacterial Sanitizing Wipes 100ct Fresh Lavender Scent
NDC: 73713-080 | Form: CLOTH
Manufacturer: Newfeel
Category: otc | Type: HUMAN OTC DRUG LABEL
Date: 20200817

ACTIVE INGREDIENTS: ALCOHOL 75 1/100 1
INACTIVE INGREDIENTS: WATER; Isopropyl Alcohol; Glycerin; ALOE VERA LEAF; ISOPROPYL MYRISTATE; Propylene Glycol; VITAMIN A PALMITATE; .ALPHA.-TOCOPHEROL ACETATE

Drug Facts

ACTIVE INGREDIENT

Ethyl Alcohol 75% v/v

INACTIVE INGREDIENTS

Water(Aqua), Isopropyl Alcohol, Glycerin, Aloe Barbadensis Leaf Juice, Isopropyl Myristate, Propylene Glycol, Retinyl Palmitate, Tocopheryl Acetate, Fragrance.

PURPOSE

Antiseptic

WARNINGS

For external use only. Flammable. Keep away from heat or flame.

When using this product avoid contact with eyes. If contact occurs, rinse eyes thoroughly with water.

Stop use and ask a doctorif irritation develops and persists for more than 72 hours.

KEEP OUT OF REACH OF CHILDREN

If swallowed, get medical help or contact a Poison Control Center right away.

Use[s]

To decrease bacteria on the skin.

Directions

For use apply thoroughly to hands and face as desired. Allow to dry without wiping. Discard wipe in trash receptacle after use. Do not flush.

For dispensing peel back front label at tab. Remove towelettes as needed. Reseal pouch by pressing label firmly back into place.